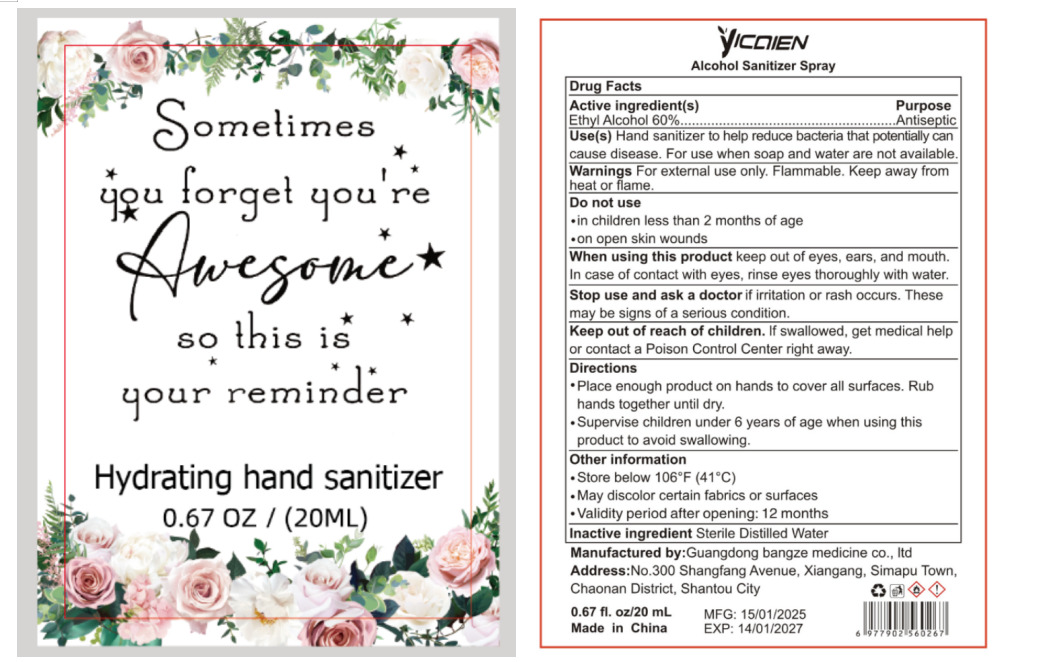 DRUG LABEL: Alcohol Sanitizer
NDC: 85279-002 | Form: SPRAY
Manufacturer: Guangdong bangze medicine co., ltd
Category: otc | Type: HUMAN OTC DRUG LABEL
Date: 20260114

ACTIVE INGREDIENTS: ALCOHOL 60 g/100 mL
INACTIVE INGREDIENTS: WATER

85279-002
Alcohol Sanitizer Spray

Active Ingredient(s)

Ethyl Alcohol 60%.

Purpose

Antiseptic

Use

Use(s) Hand sanitizer to help reduce bacteria that potentially can cause disease. For use when soap and water are not available.

Warnings

Warnings For external use only. Flammable. Keep away from heat or flame.

Do not use

●in children less than 2 months of age
●on open skin wounds

When using this product keep out of eyes, ears, and mouth. In case of contact with eyes, rinse eyes thoroughly with water.

Stop use and ask a doctor if irritation or rash occurs. These may be signs of a serious condition.

Keep out of reach of children. If swallowed, get medical help or contact a Poison Control Center right away.

Directions

●Place enough product on hands to cover all surfaces. Rub hands together until dry.
●Supervise children under 6 years of age when using this product to avoid swallowing.

Other information

●Store below 106°F (41°C)
●May discolor certain fabrics or surfaces
●Validity period after opening: 12 months

Inactive ingredients

Sterile Distilled Water